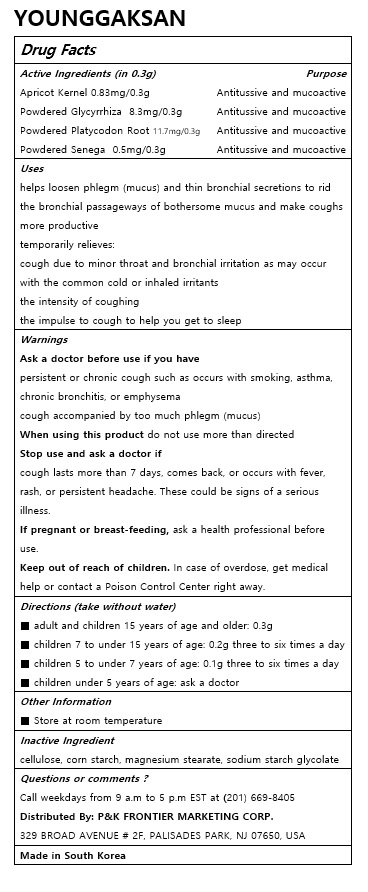 DRUG LABEL: YOUNGGAKSAN
NDC: 72988-0020 | Form: POWDER
Manufacturer: LYDIA Co., Ltd
Category: otc | Type: HUMAN OTC DRUG LABEL
Date: 20191008

ACTIVE INGREDIENTS: PLATYCODON GRANDIFLORUS ROOT 11.7 mg/0.3 g; POLYGALA SENEGA ROOT 0.5 mg/0.3 g; APRICOT KERNEL OIL 0.83 mg/0.3 g; GLYCYRRHIZIN 8.3 mg/0.3 g
INACTIVE INGREDIENTS: POWDERED CELLULOSE; MAGNESIUM STEARATE; STARCH, CORN; SODIUM STARCH GLYCOLATE TYPE A CORN

ACTIVE INGREDIENT

Apricot Kernel

Powdered Glycyrrhiza

Powdered Platycodon Root

Powdered Senega

PURPOSE

helps loosen phlegm (mucus) and thin bronchial secretions to rid the bronchial passageways of bothersome mucus and make coughs more productive

temporarily relieves:

cough due to minor throat and bronchial irritation as may occur with the common cold or inhaled irritants

the intensity of coughing

the impulse to cough to help you get to sleep

Keep out of reach of children

INDICATIONS AND USAGE

Directions (take without water)

■ adult and children 15 years of age and older: 0.3g

■ children 7 to under 15 years of age: 0.2g three to six times a day

■ children 5 to under 7 years of age: 0.1g three to six times a day

■ children under 5 years of age: ask a doctor

Ask a doctor before use if you have

persistent or chronic cough such as occurs with smoking, asthma, chronic bronchitis, or emphysema

cough accompanied by too much phlegm (mucus)

When using this product do not use more than directed

Stop use and ask a doctor if

cough lasts more than 7 days, comes back, or occurs with fever, rash, or persistent headache. These could be signs of a serious illness.

If pregnant or breast-feeding, ask a health professional before use.

Keep out of reach of children. In case of overdose, get medical help or contact a Poison Control Center right away.

INACTIVE INGREDIENT

cellulose, corn starch, magnesium stearate, sodium starch glycolate

DOSAGE AND ADMINISTRATION

For oral use only